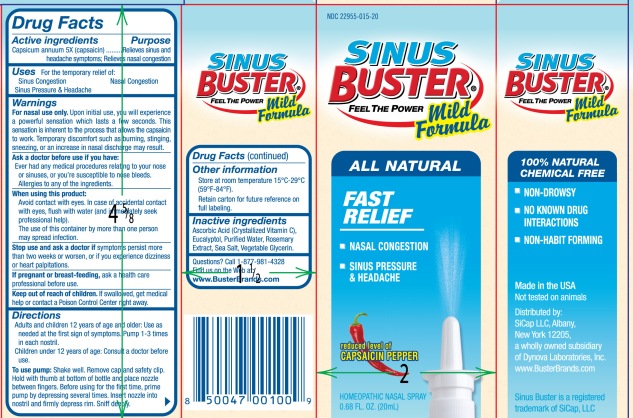 DRUG LABEL: Sinus Buster Mild Formula
NDC: 22955-015 | Form: SPRAY
Manufacturer: SiCap Industries LLC
Category: homeopathic | Type: HUMAN OTC DRUG LABEL
Date: 20100421

ACTIVE INGREDIENTS: RED PEPPER 5 [hp_X]/20 mL

PURPOSE

Capsicum annuum........Relieves sinus and headache symptoms; relieves nasal congestion

INDICATIONS AND USAGE

Uses: For the Temporary Relief of:

- Sinus Congestion
- Nasal Congestion
- Sinus Pressure and Headache

WARNINGS

For nasal use only. Upon initial use, you will experience a powerful sensation which lasts a few seconds. This sensation is inherent to the process that allows the capsaicin to work. Temporary discomfort such as burning, stinging, sneezing, or an increase in nasal discharge may result.

Ask a doctor before use if you have:

- ever had any medical procedures relating to your nose or sinuses, or you're susceptible to nose bleeds
- allergies to any of the ingredients.

When using this product:

- Avoid contact with the eyes, In case of accidental contact with eyes, flush with water (and immediately seek professional help).
- The use of this container by more than one person may spread infection.

Stop use and ask doctor if symptoms persist more than two weeks or worsen or if you experience dizziness or hear palpitations.

PREGNANCY OR BREAST FEEDING

If pregnant or breast-feeding, ask a health care professional before use.

Keep out of reach of children. If swallowed get medical help or contact a Poison Control Center right away.

Directions:

- Adults and children 12 years of age and older: use as needed at the first sign of symptoms. Pump 1-3 times in each nostril.
- Children under 12 years of age: Consult a doctor before use.

To use pump: Shake well. Remove cap and safety clip. Hold with thumb at bottom of bottle and place nozzle between fingers. Before using the first time, prime pump by depressing several times. Insert nozzle into nostril and firmly depress rim. Sniff deeply.

STORAGE AND HANDLING

- Store at room temperature 15-29 degrees C (59-84 degrees F)
- Retain carton for future reference on full labeling

INACTIVE INGREDIENT

Ascorbic Acid (Crystallized Vitamin C), Eucalyptol, Purified Water, Rosemary Extract, Sea Salt, Vegetable Glycerin

Questions? Call 1-877-981-4328
Find us on the web at: www.BusterBrands.com

PACKAGE LABEL

100% Natural Chemical Free
Non-drowsy
No Known Drug Interactions
Non-habit Forming
Fast Relief

- Nasal Congestion
- Sinus Pressure and Headache

reduced level of Capsaicin Pepper

Made in the USA
Not tested on Animals
Distributed by:
SiCap LLC
Albany New York 12205
A wholly owned subsidiary of Dynova Laboratories
www.BusterBrands.com